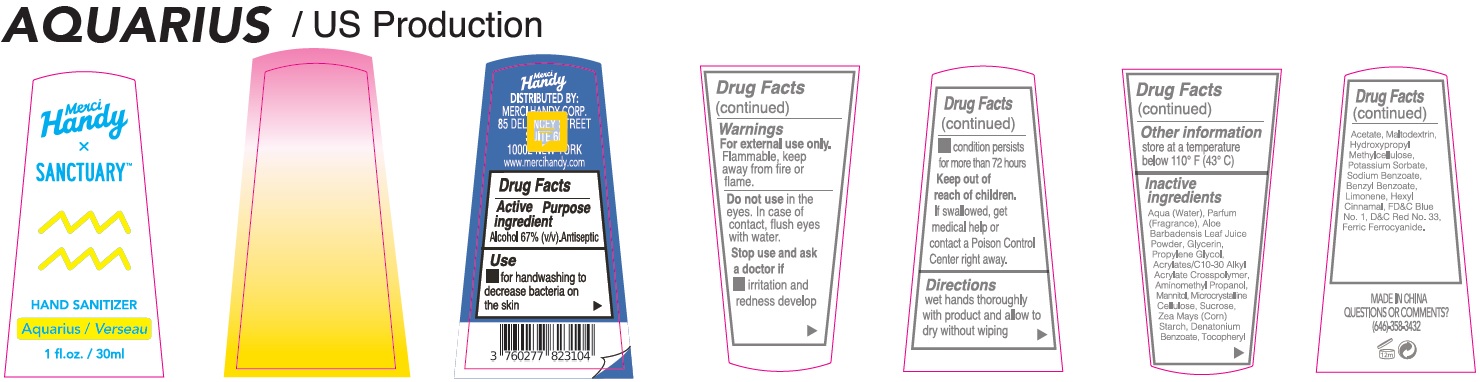 DRUG LABEL: Merci Handy Sanctuary Hand Sanitizer AQUARIUS
NDC: 72866-028 | Form: GEL
Manufacturer: MERCI HANDY CORPORATION
Category: otc | Type: HUMAN OTC DRUG LABEL
Date: 20221201

ACTIVE INGREDIENTS: ALCOHOL 67 mL/100 mL
INACTIVE INGREDIENTS: WATER; ALOE VERA LEAF; GLYCERIN; PROPYLENE GLYCOL; CARBOMER INTERPOLYMER TYPE A (ALLYL SUCROSE CROSSLINKED); AMINOMETHYLPROPANOL; MANNITOL; MICROCRYSTALLINE CELLULOSE; SUCROSE; CORN; DENATONIUM BENZOATE; .ALPHA.-TOCOPHEROL ACETATE; MALTODEXTRIN; HYPROMELLOSE, UNSPECIFIED; POTASSIUM SORBATE; SODIUM BENZOATE; BENZYL BENZOATE; LIMONENE, (+)-; .ALPHA.-HEXYLCINNAMALDEHYDE; FD&C BLUE NO. 1; D&C RED NO. 33; FERRIC FERROCYANIDE

Merci Handy Sanctuary Hand Sanitizer AQUARIUS

Active ingredient

Alcohol 67% (v/v)

Purpose

Antiseptic

Use

- for handwashing to decrease bacteria on the skin

Warnings

For external use only.

Flammable, keep away from fire or flame.

Do not use

in the eyes. In the case of contact, flush eyes with water.

Stop use and ask a doctor if

- irritation and redness develop
- condition persists for more than 72 hours

Keep out of reach of children.

If swallowed, get medical help or contact a Poison Control Center right away

Directions

wet hands thoroughly with product and allow to dry without wiping

Other information

store at a temperature below 110° F (43° C)

Inactive Ingredients

Aqua (Water), Parfum (Fragrance), Aloe Barbadensis Leaf Juice Powder, Glycerin, Propylene Glycol, Acrylates/C10-30 Alkyl Acrylate Crosspolymer, Aminomethyl Propanol, Mannitol, Microcrystalline Cellulose, Sucrose, Zea Mays (Corn) Starch, Denatonium Benzoate, Tocopheryl Acetate, Maltodextrin, Hydroxypropyl Methylcellulose, Potassium Sorbate, Sodium Benzoate, Benzyl Benzoate, Limonene, Hexyl Cinnamal, FD&C Blue No. 1, D&C Red No. 33, Ferric Ferrocyanide.

QUESTIONS OR COMMENTS?

(646)-358-3432